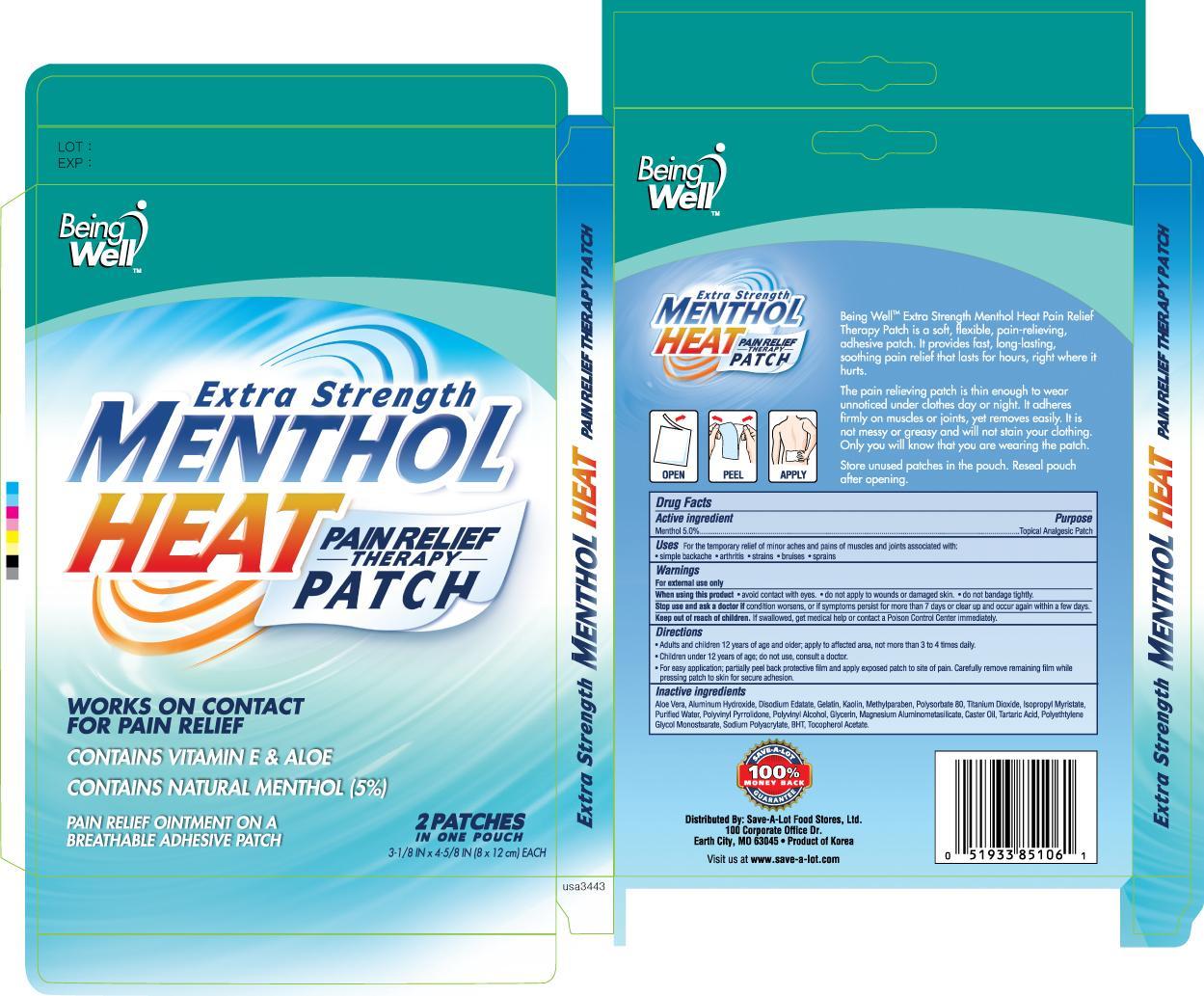 DRUG LABEL: Being Well Extra Strength Menthol Heat
                
NDC: 46994-851 | Form: PATCH
Manufacturer: SAVE-A-LOT FOOD STORES, LTD.
Category: otc | Type: HUMAN OTC DRUG LABEL
Date: 20130630

ACTIVE INGREDIENTS: MENTHOL 750 mg/1 1
INACTIVE INGREDIENTS: ALOE VERA LEAF; ALUMINUM HYDROXIDE; GELATIN; KAOLIN; METHYLPARABEN; POLYSORBATE 80; TITANIUM DIOXIDE; ISOPROPYL MYRISTATE; WATER; POLYVINYL ALCOHOL; TARTARIC ACID; BUTYLATED HYDROXYTOLUENE; ALPHA-TOCOPHEROL ACETATE

Drug Facts

Active ingredient Purpose

Menthol 5.0%......................................................Topical Analgesic Patch

PURPOSE

Uses For the temporary relief of minor aches and pains of muscles and joints associated with:

- simple backache
- arthritis
- strains
- bruises
- sprains

Warnings for external use only

When using this product

- avoid contact with eyes
- do not apply to wounds or damaged skin
- do not bandage tightly

Stop use and ask a doctor if condition worsens, or if symptoms persist for more than 7 days or clear up and occur again within a few days

Keep out of reach of children if swallowed, get medical help or contact a Poison Control Center immediately

Directions

- Adults and children 12 years of age and over: apply to affected area, not more than 3 to 4 times daily
- Children under 12 years of age: do not use, consult a doctor
- For easy application: partially peel back protective film and apply exposed patch to site of pain. Carefully remove remaining film while pressing patch to skin for secure adhesion.

INACTIVE INGREDIENT

Inactive ingredients Aloe Vera, Aluminum Hydroxide, Disodium Edatate, Gelatin, Kaolin, Methylparaben, Polysorbate 80, Titanium Dioxide, Isopropyl Myristate, Purified Water, Polyvinyl Pyrrolidone, Polyvinyl Alcohol, Glycerin, Magnesium Aluminometasilicate, Caster Oil, Tartaric Acid, Polyethylene Glyco Monostearate, Sodium Polyacrylate, BHT, Tocopherol Acetate

DOSAGE AND ADMINISTRATION

Distributed By:

Save-A-Lot Food Stores, Ltd.

100 Corporate Office Dr.

Earth City, MO 63045

Product of Korea